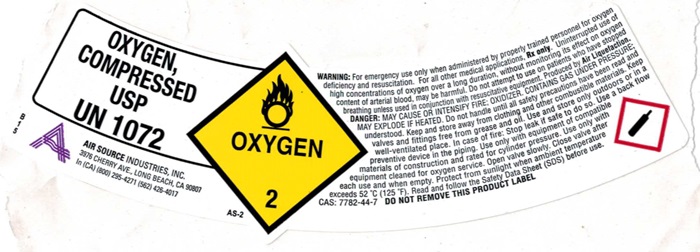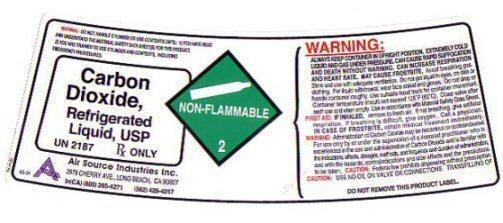 DRUG LABEL: CARBON DIOXIDE
NDC: 10167-500 | Form: GAS
Manufacturer: Air Source Industries Inc
Category: prescription | Type: HUMAN PRESCRIPTION DRUG LABEL
Date: 20241006

ACTIVE INGREDIENTS: CARBON DIOXIDE 99 L/100 L

Carbon Dioxide

CARBON DIOXIDE USP Product Label

CARBON DIOXIDE USP UN 1013 RX ONLY

E15 A AIR SOURCE INDUSTRIES, INC.

3976 CHERRY AVE., LONG BEACH, CA 90807

In CA (800) 295-427 (562) 426-4017

NON-FLAMMABLR GAS 2 AS-6

WARNING: Administration of Carcon Dioxide may be hazardous or contraindicated. For Use only by or under the supervision of a licensed practitioner who is experienced in the use and administration of Carbon Dioxide and is familiar with the indications, effects, dosages, methods, and frequency and duration of administration, and with the hazards, contraindications and side effects, and the precautions to be taken. WARNING: CONTAINS GAS UNDER PRESSURE: MAY EXPLODE IF HEATED. MAY DISPLACE OXYGEN AND CAUSE RAPID SUFFOCATION. Do not handle until all safety precautions have been read and understood. Use and store only outdoors or in a well-ventilated place. Use a back flow preventive device in the piping. Use only with equipment rated for cylinder pressure. Close valve after each use and when empty. Protect from sunlight when ambient temperature exceeds 52°C (125°F). Read and follow the Safety Data Sheet (SDS) before use. FIRST AID: IF INHALED: Remove person to fresh air and keep comfortable for breathing. Get medical advice/attention.

CAS 124-38-9 DO NOT REMOVE THIS PRODUCT LABEL

CARBON DIOXIDE Refrigerated Liquid, USP Product Label

CARBON DIOXIDE, Refrigerated Liquid, USP UN 2187 Rx ONLY

G08 AS-31

A AIR SOURCE INDUSTRIES, INC.

3976 CHERRY AVE., LONG BEACH, CA 90807

In CA (800) 295-427 (562) 426-4017

NON-Flammable 2

WARNING:

ALWAYS KEEP CONTAINER IN UPRIGHT POSITION. EXTREMELY COLD LIQUID AND GAS PRESSURE. CAN CAUSE RAPID SUFFOCATION AND DEATH WITHOUT WARNING. CAN INCREASE RESPIRATION AND HEART RATE. MAY CAUSE FROSTBITE. Avoid breathing gas. Store and use with adequate ventilation. Do not get liquid in eyes on skin, or clothing. For liquid withdraw, wear face shield and gloves. Do not drop or handle container roughly. Use suitable hand truck for container movement. Container temperature should not exceed 125°F (52°C). Close valve after each use and when empty. Use in accordance with Material Safety Data Sheet. FIRST AID: IF INHALED, remove to fresh air. If not breathing, give artificial respiration. If breathing is difficult, give oxygen. Call a physician. IN CASE OF FROSTBITE, obtain medical treatment immediately. WARNING: Administration of Carbon Dioxide may be hazardous or contraindicated. For use only by or under the supervision of a licensed practitioner who is experienced in the use and administration of Carbon Dioxide and is familiar with the indications, effects, dosages, methods, and frequency and duration of administration, and with the hazards, contraindications and side effects and the precautions to be taken. CAUTION: Federal law prohibits dispensing without prescription. CAUTION: USE NO OIL ON VALVE OR CONNECTIONS: TRANSFILING OF

DO NOT REMOVE THIS PRODUCT LABEL